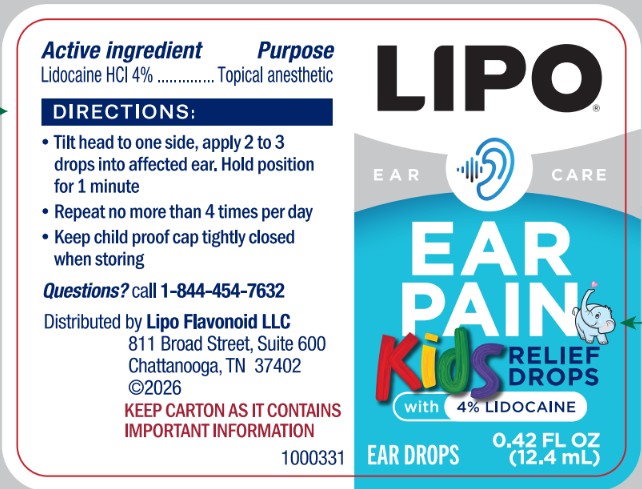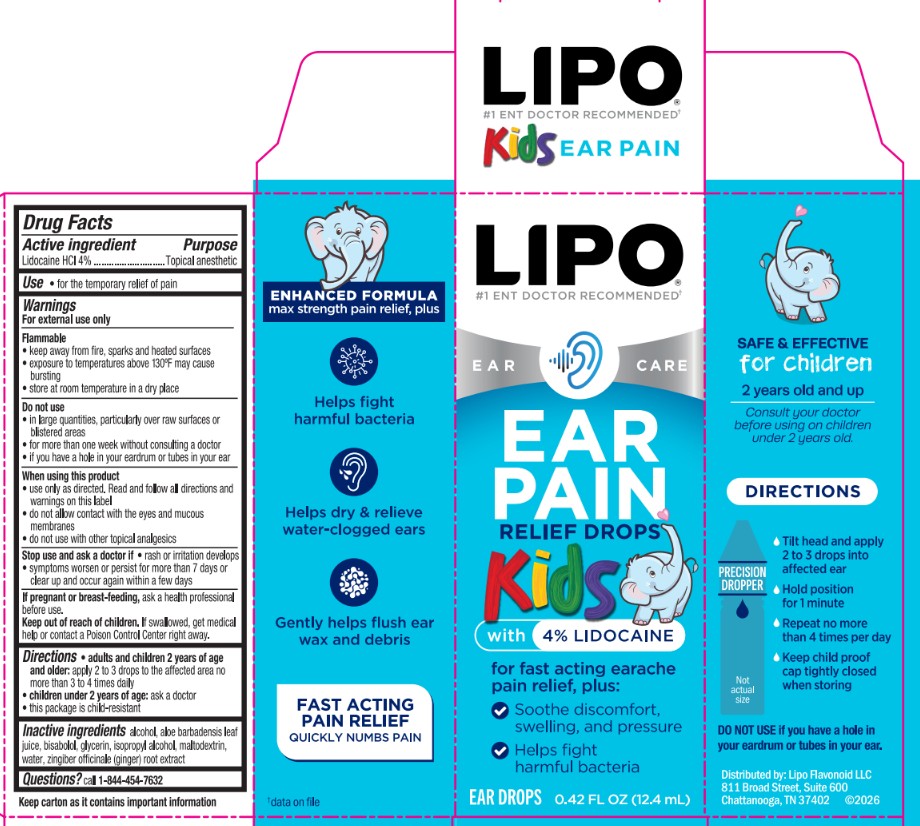 DRUG LABEL: Lipoflavonoid Ear Pain Kids Relief Drops
NDC: 69693-902 | Form: LIQUID
Manufacturer: Clarion Brands LLC
Category: otc | Type: HUMAN OTC DRUG LABEL
Date: 20251030

ACTIVE INGREDIENTS: LIDOCAINE HCL 4 g/100 mL
INACTIVE INGREDIENTS: WATER; GLYCERIN; ALCOHOL; BISABOLOL; ZINGIBER OFFICINALE (GINGER) ROOT OIL; ALOE VERA LEAF JUICE

ACTIVE INGREDIENT

Lidocaine HCl 4%

PURPOSE

Topical anesthetic

INDICATIONS AND USAGE

For the temporary relief of pain

WARNINGS

For external use only

Flammable

- keep away from fire, sparks, and heated surfaces
- exposure to temperatures above 130 degress F may cause bursting
- store at room temperature in a dry place

Do not use

- in large quantities, particularly over raw surfaces or blistered areas
- for more than one week without consulting a doctor
- if you have a hole in your ear drum or tubes in your ear

When using this product

- use only as directed. Read and follow all directions and warning on this label.
- do not allow contact with the eyes and mucous membranes
- do not use with other topical analgesics

Stop use and ask a doctor if

- rash or irritation develops
- symptoms worsen or persist for more than 7 days or clear up and occur again within a few days

WHEN USING

- Use only as directed. Read and follow all directions and warning on this label
- do not allow contact wtih the eyes and mucous membranes
- do not use with other topical analgesics

INACTIVE INGREDIENT

alcohol

aloe barbadensis leaf juice

bisabolol

glycerin

isopropyl alcohol

maltodextrin

water

zingiber officinale (ginger) root extract

QUESTIONS

call 1-844-454-7632

DOSAGE AND ADMINISTRATION

Lidocaine HCl 4%

Topical anesthetic

Directions

- adults and chilren 2 years of age and older: apply 2 to 3 drops to the affected area no more than 3 to 4 times daily
- children under 2 years of age: ask a doctor
- this package is child-resistant

PACKAGE LABEL

Lipo #1 ENT Doctor Recommended

Ear Pain Relief Drops

Kids with 4% Lidocaine

for fast acting earache pain relief, plus:

- Soothe discomfort, swelling, and pressure
- Helps fight harmful bacteria

EAR DROPS 0.42 FL OZ (12.4mL)

Enhanced Formula max strength pain relief, plus

Helps fight harmful bacteria

Helps dry & relieve water-clogged ears

Gently helps flush ear wax and debris

FAST ACTING PAIN RELIEF

Quickly Numbs Pain

SAFE & EFFECTIVE for Children 2 years old and up

Consult your doctor before using on children under 2 years old.

DIRECTIONS

Tilt head and apply 2 to 3 drops into affected ear

Hold position for 1 minute

Repeat no more than 4 times per day

Keep child proof cap tightly closed when storing

DO NOT USE if you have a hole in your eardrum or tubes in your ear.

Distributed by: Lipo Flavonoid LLC

811 Broad Street, Suite 600

Chattanooga, TN 37402